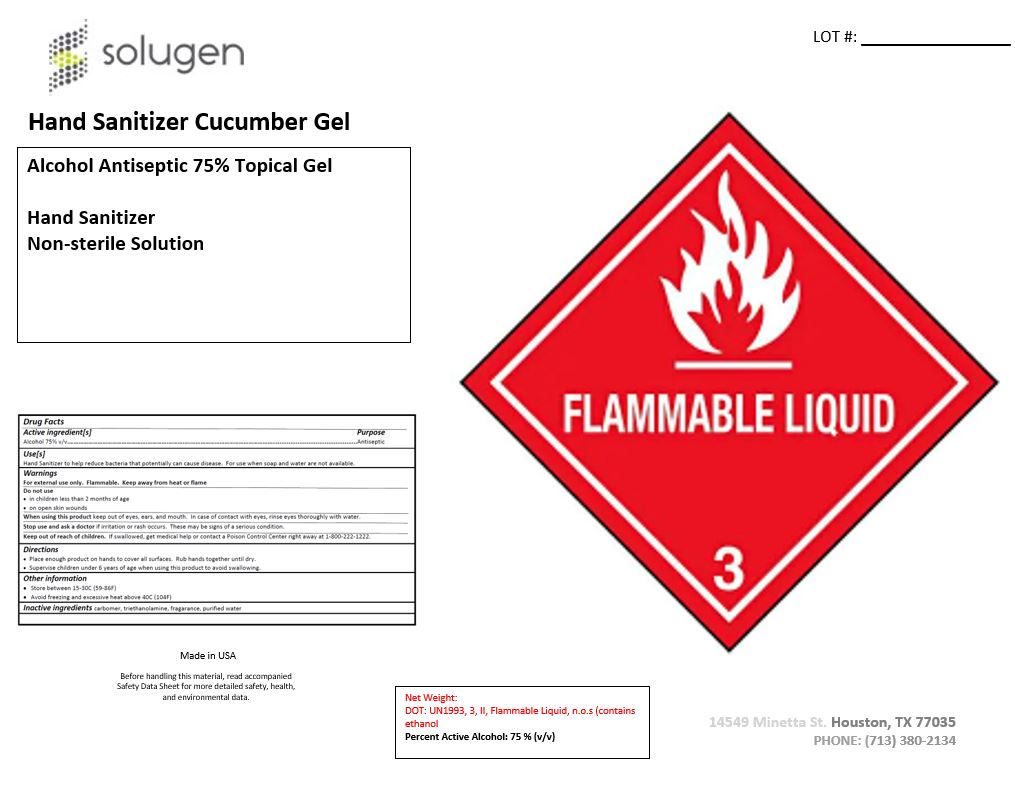 DRUG LABEL: Hand Sanitizer Cucumber Gel 75% Alcohol Antiseptic
NDC: 79975-007 | Form: GEL
Manufacturer: Solugen Blending LLC
Category: otc | Type: HUMAN OTC DRUG LABEL
Date: 20200909

ACTIVE INGREDIENTS: ALCOHOL 75 mL/100 mL
INACTIVE INGREDIENTS: HYDROXYMETHYL CELLULOSE; WATER; 3-(3,4-METHYLENEDIOXYPHENYL)-2-METHYLPROPANAL; CARBOMER 940; .ALPHA.-AMYLCINNAMALDEHYDE; TROLAMINE

Hand Sanitizer Cucumber Gel 75% Alcohol Antiseptic Topical

Active Ingredient(s)

Alcohol 75% v/v. Purpose: Antiseptic

Purpose

Antiseptic, Hand Sanitizer

Use

Hand Sanitizer to help reduce bacteria that potentially can cause disease. For use when soap and water are not available.

Warnings

For external use only. Flammable. Keep away from heat or flame

Do not use

- in children less than 2 months of age
- on open skin wounds

When using this product keep out of eyes, ears, and mouth. In case of contact with eyes, rinse eyes thoroughly with water.
Stop use and ask a doctor if irritation or rash occurs. These may be signs of a serious condition.
Keep out of reach of children. If swallowed, get medical help or contact a Poison Control Center right away at 1-800-222-1222.

Stop use and ask a doctor if irritation or rash occurs. These may be signs of a serious condition.

Keep out of reach of children. If swallowed, get medical help or contact a Poison Control Center right away at 1-800-222-1222.

Directions

- Place enough product on hands to cover all surfaces. Rub hands together until dry.
- Supervise children under 6 years of age when using this product to avoid swallowing.

Other information

- Store between 15-30C (59-86F)
- Avoid freezing and excessive heat above 40C (104F)

Inactive ingredients

carbomer, triethanolamine, fragrance, purified water USP

Hand Sanitizer Cucumber Gel 75% Alcohol Antiseptic

18927000 mL NDC: 79975-007-01